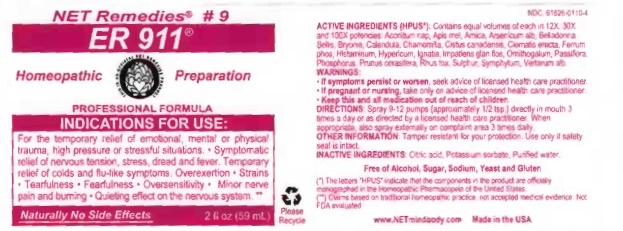 DRUG LABEL: ER 911
NDC: 61626-0110 | Form: LIQUID
Manufacturer: Net Remedies
Category: homeopathic | Type: HUMAN PRESCRIPTION DRUG LABEL
Date: 20210121

ACTIVE INGREDIENTS: ACONITUM NAPELLUS 12 [hp_X]/59.1 mL; APIS MELLIFERA 12 [hp_X]/59.1 mL; ARNICA MONTANA 12 [hp_X]/59.1 mL; ARSENIC TRIOXIDE 12 [hp_X]/59.1 mL; ATROPA BELLADONNA 12 [hp_X]/59.1 mL; BELLIS PERENNIS 12 [hp_X]/59.1 mL; BRYONIA ALBA ROOT 12 [hp_X]/59.1 mL; CALENDULA OFFICINALIS FLOWERING TOP 12 [hp_X]/59.1 mL; MATRICARIA CHAMOMILLA 12 [hp_X]/59.1 mL; HELIANTHEMUM CANADENSE 12 [hp_X]/59.1 mL; CLEMATIS RECTA FLOWERING TOP 12 [hp_X]/59.1 mL; FERROSOFERRIC PHOSPHATE 12 [hp_X]/59.1 mL; HISTAMINE DIHYDROCHLORIDE 12 [hp_X]/59.1 mL; HYPERICUM PERFORATUM 12 [hp_X]/59.1 mL; STRYCHNOS IGNATII SEED 12 [hp_X]/59.1 mL; IMPATIENS GLANDULIFERA FLOWER 12 [hp_X]/59.1 mL; ORNITHOGALUM UMBELLATUM 12 [hp_X]/59.1 mL; PASSIFLORA INCARNATA FLOWERING TOP 12 [hp_X]/59.1 mL; PHOSPHORUS 12 [hp_X]/59.1 mL; PRUNUS CERASIFERA FLOWER 12 [hp_X]/59.1 mL; TOXICODENDRON PUBESCENS LEAF 12 [hp_X]/59.1 mL; SULFUR 12 [hp_X]/59.1 mL; COMFREY ROOT 12 [hp_X]/59.1 mL; VERATRUM ALBUM ROOT 12 [hp_X]/59.1 mL
INACTIVE INGREDIENTS: CITRIC ACID MONOHYDRATE; POTASSIUM SORBATE; WATER

ER 911

ACTIVE INGREDIENT

ACTIVE INGREDIENTS (HPUS*): Contains equal volumes of each in 12X, 30X, and 100X potencies: Aconitum nap, Apis mel, Arnica, Arsenicum alb, Belladonna, Bellis, Bryonia, Calendula, Chamomilla, Cistus canadensis, Clematis erecta, Ferrum phos, Histaminum, Hypericum, Ignatia, Impatiens glan flos, Orithogalum, Passiflora, Phosphorus, Prunus cerasifera, Rhus tox, Sulphur, Symphytum, Veratrum alb.

(*) The letters "HPUS" indicate that the components in the product are officially monographed in the Homeopathic Pharmacopeia of the United States.

(**) Claims based on traditional homeopathic practice, not accepted medical evidence. Not FDA evaluated.

INDICATIONS AND USAGE

INDICATIONS FOR USE: For the temporary relief of emotional, mental, or physical trauma, high pressure or stressful situations • Symptomatic relief of nervous tension, stress, dread and fever. Temporary relief of cold and flu-like symptoms. Overexertion • Strains • Tearfulness • Fearfulness • Oversensitivity • Minor nerve pain and burning • Quieting effect on nervous system.**

WARNINGS:

• If sumptoms persist or worsen, seek advice of licensed health care practitioner.

• If pregnant or nursing, take on advice of licensed health care practitioner.

• Keep this and all medication out of reach of children.

KEEP OUT OF REACH OF CHILDREN

• Keep this and all medication out of reach of children.

DOSAGE AND ADMINISTRATION

DIRECTIONS: Spray 9-12 pumps (approximately 1/2 tsp.) directly in mouth 3 times a day or as direced by licensed health care practitioner. When appropriate, also spray externally on complaint area 3 times daily.

OTHER INFORMATION: Tamper resistant for your protection. Use only if safetly seal is intact.

INACTIVE INGREDIENTS: Citric acid, Potassium sorbate, Purified water.

Free of Alcohol, Sugar, Yeast and Gluten.

QUESTIONS

www.NETmindbody.com

Made in the USA

PACKAGE LABEL

NET Remedies #9

ER 911

Homeopathic PreparationPROFESSIONAL FORMULA

Naturally No Side Effects

PURPOSE

INDICATIONS FOR USE: For the temporary relief of emotional, mental, or physical trauma, high pressure or stressful situations • Symptomatic relief of nervous tension, stress, dread and fever. Temporary relief of cold and flu-like symptoms. Overexertion • Strains • Tearfulness • Fearfulness • Oversensitivity • Minor nerve pain and burning • Quieting effect on nervous system.**